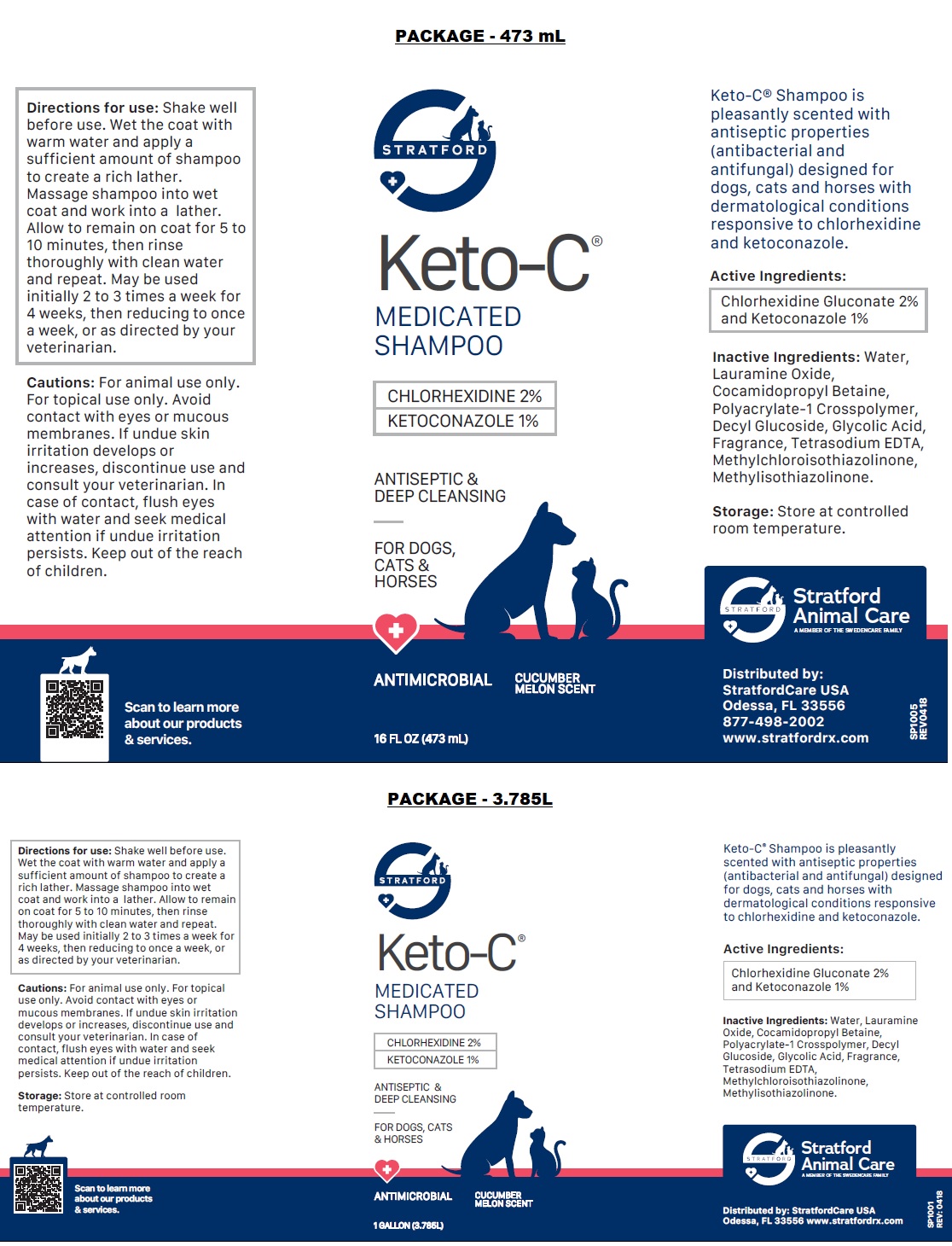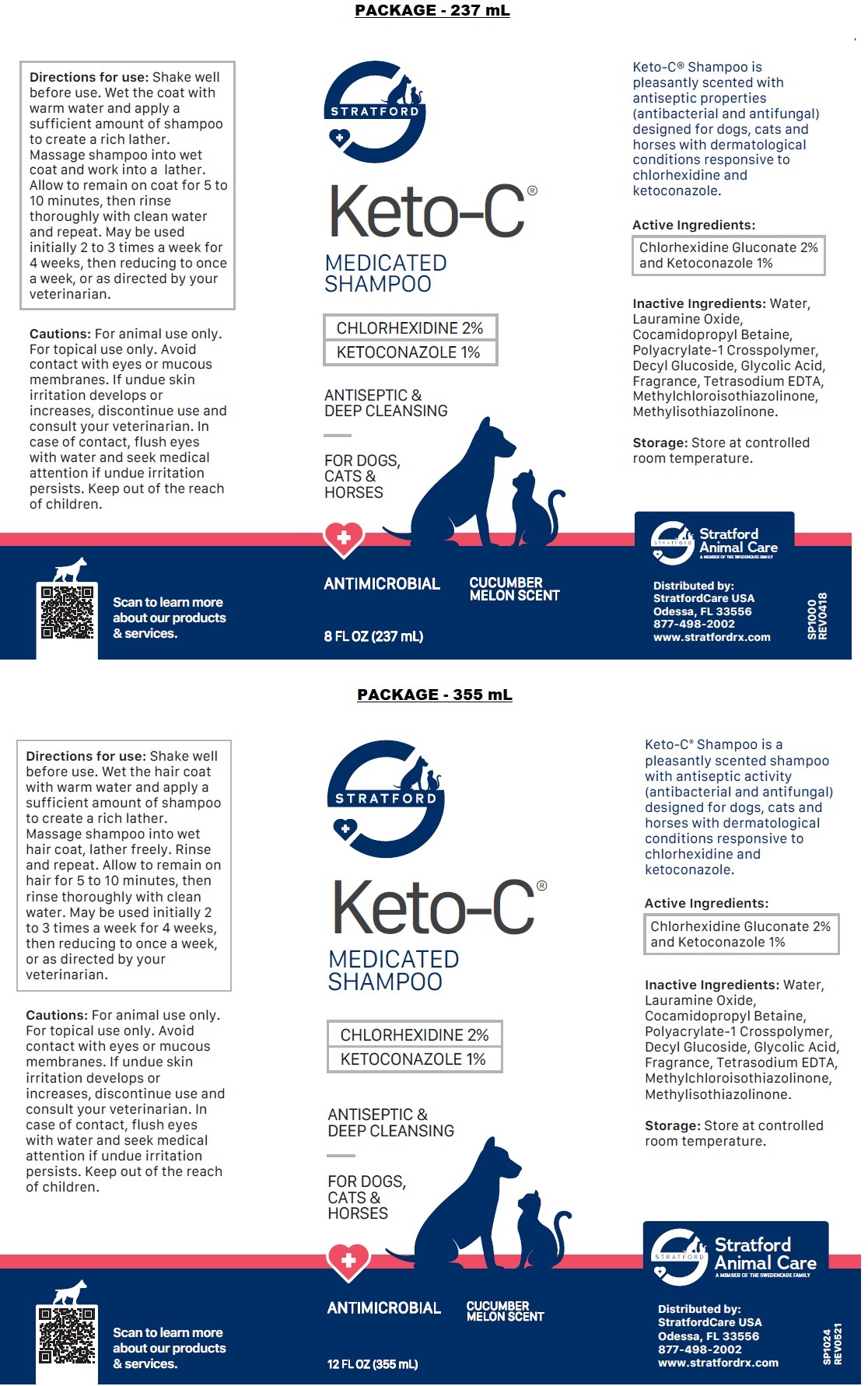 DRUG LABEL: Keto-C
NDC: 86069-100 | Form: SHAMPOO
Manufacturer: Stratford Care Usa, Inc.
Category: animal | Type: OTC ANIMAL DRUG LABEL
Date: 20221108

ACTIVE INGREDIENTS: CHLORHEXIDINE GLUCONATE 2 g/100 mL; KETOCONAZOLE 1 g/100 mL
INACTIVE INGREDIENTS: WATER; LAURAMINE OXIDE; COCAMIDOPROPYL BETAINE; POLYACRYLATE-1 CROSSPOLYMER; DECYL GLUCOSIDE; GLYCOLIC ACID; EDETATE SODIUM; METHYLCHLOROISOTHIAZOLINONE; METHYLISOTHIAZOLINONE

Keto-C® MEDICATED SHAMPOO

Active Ingredients:

Chlorhexidine Gluconate 2% and Ketoconazole 1%.

PURPOSE

antibacterial and antifungal

INDICATIONS AND USAGE

Keto-C® Shampoo is pleasantly scented with antiseptic properties (antibacterial and antifungal) designed for dogs, cats and horses with dermatological conditions responsive to chlorhexidine and ketoconazole.

INACTIVE INGREDIENT

Inactive Ingredients: Water, Lauramine Oxide, Cocamidopropyl Betaine, Polyacrylate-1 Crosspolymer, Decyl Glucoside, Glycolic Acid, Fragrance, Tetrasodium EDTA, Methylchloroisothiazolinone, Methylisothiazolinone.

Storage: Store at controlled room temperature.

DOSAGE AND ADMINISTRATION

Directions for use: Shake well before use. Wet the coat with warm water and apply a sufficient amount of shampoo to create a rich lather. Massage shampoo into wet coat and work into a lather. Allow to remain on coat for 5 to 10 minutes, then rinse thoroughly with clean water and repeat. May be used initially 2 to 3 times a week for 4 weeks, then reducing to once a week, or as directed by your veterinarian.

PRECAUTIONS

Cautions: For animal use only. For topical use only. Avoid contact with eyes or mucous membranes. If undue skin irritation develops or increases, discontinue use and consult your veterinarian. In case of contact, flush eyes with water and seek medical attention if undue irritation persists. Keep out of the reach of children.

MEDICATED SHAMPOO

ANTISEPTIC & DEEP CLEANSING

FOR DOGS, CATS & HORSES

ANTIMICROBIAL

CUCUMBER MELON SCENT

Stratford Animal Care
A MEMBER OF THE SWEDENCARE FAMILY

Distributed by:
StratfordCare USA
Odessa, FL 33556
877-498-2002
www.stratfordrx.com